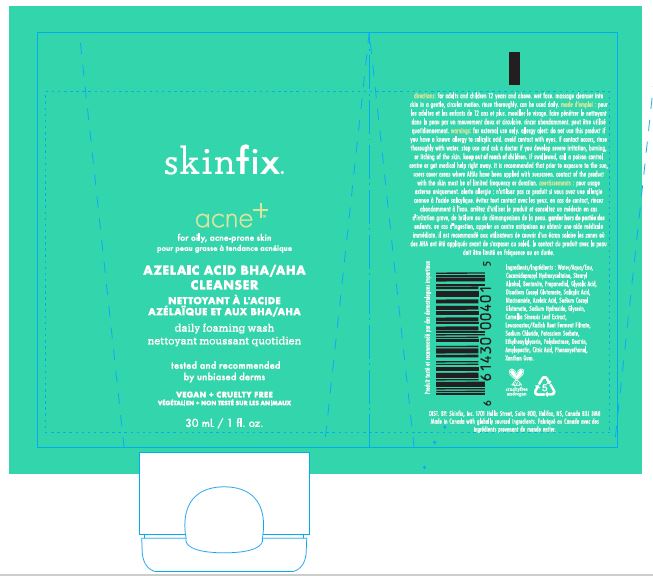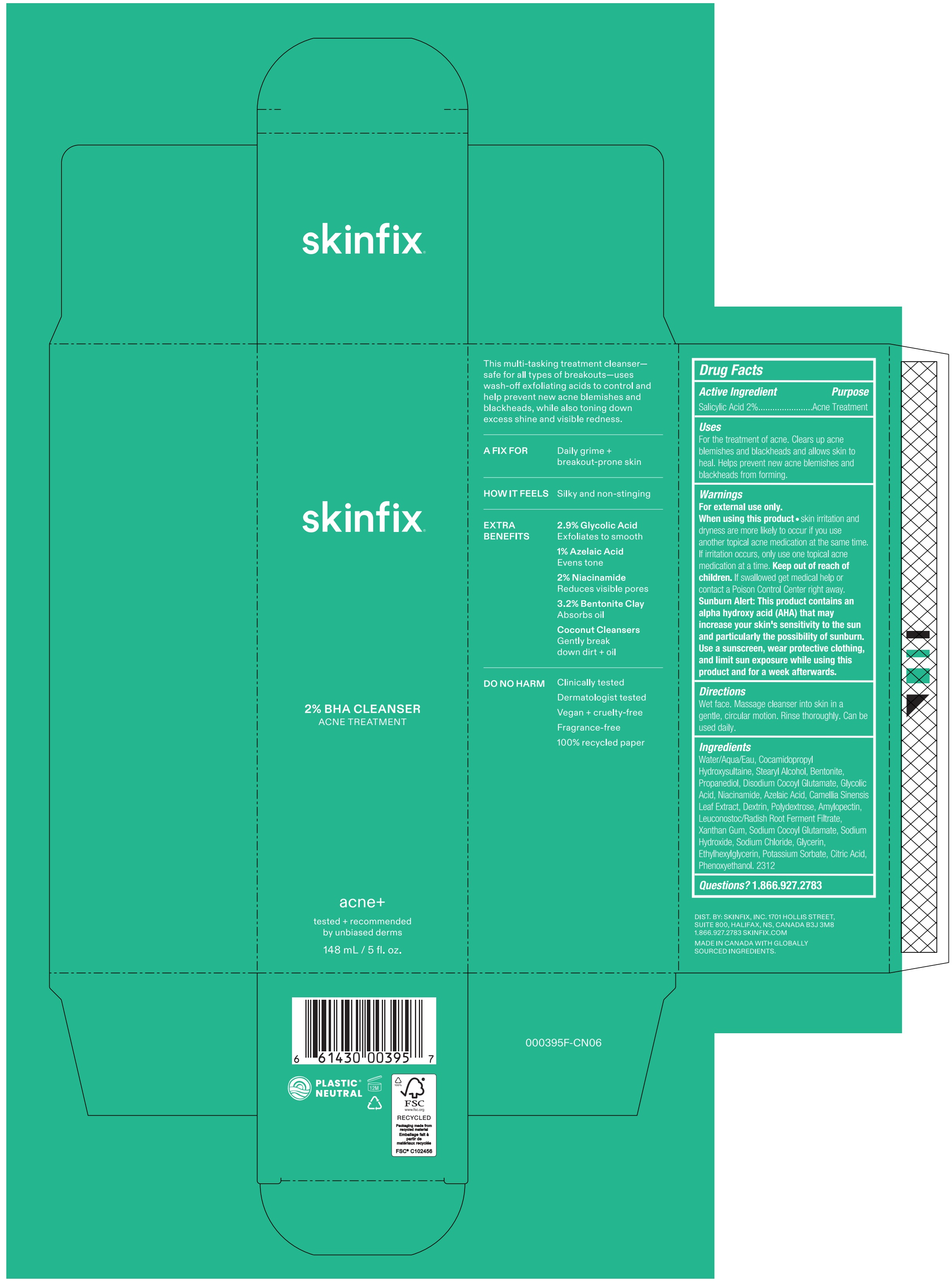 DRUG LABEL: BHA CLEANSER
NDC: 61328-403 | Form: LOTION
Manufacturer: Skinfix, Inc.
Category: otc | Type: HUMAN OTC DRUG LABEL
Date: 20260112

ACTIVE INGREDIENTS: SALICYLIC ACID 2 g/100 mL
INACTIVE INGREDIENTS: WATER; COCAMIDOPROPYL HYDROXYSULTAINE; STEARYL ALCOHOL; PROPANEDIOL; DISODIUM COCOYL GLUTAMATE; GLYCOLIC ACID; BENTONITE; NIACINAMIDE; SODIUM HYDROXIDE; AZELAIC ACID; GREEN TEA LEAF; GLYCERIN; ETHYLHEXYLGLYCERIN; POLYDEXTROSE; ICODEXTRIN; AMYLOPECTIN, UNSPECIFIED SOURCE; SODIUM COCOYL GLUTAMATE; XANTHAN GUM; ANHYDROUS CITRIC ACID; POTASSIUM SORBATE; PHENOXYETHANOL; SODIUM BENZOATE

SKINFIX - ACNE+ 2% BHA CLEANSER

Active Ingredient

SALICYLIC ACID 2%

Purpose

ACNE TREATMENT

USES

HELPS CLEAR ACNE BLEMISHES AND ALLOWS SKIN TO HEAL. HELPS KEEP SKIN CLEAR OF NEW ACNE BLEMISHES. HELPS PREVENT NEW ACNE BLEMISHES FROM FORMING.

WARNINGS

FOR EXTERNAL USE ONLY.

WHEN USING THIS PRODUCT

- SKIN IRRITATION AND DRYNESS IS MORE LIKELY TO OCCUR IF YOU USE ANOTHER TOPICAL ACNE MEDICATION AT THE SAME TIME. IF IRRITATION OCCURS, ONLY USE ONE TOPICAL ACNE MEDICATION AT A TIME.

Keep out of reach of children. If swallowed get medical help or contact a Poison Control Center right away

Directions

DISPENSE A PEA-SIZED AMOUNT ONTO DAMP PALMS AND WORK INTO A LATHER. MASSAGE OVER FACE AND NECK IN AN OUTWARD, CIRCULAR MOTIONS, CONCENTRATING ON OILY AND BREAKOUT-PRONE AREAS. RINSE THOROUGHLY WITH WARM WATER.

ALLERGY ALERT DO NOT USE THIS PRODUCT IF YOU HAVE A KNOWN ALLERGY TO SALICYLIC ACID.

Inactive Ingredients

WATER (EAU), COCAMIDOPROPYL HYDROXYSULTAINE, STEARYL ALCOHOL, PROPANEDIOL, DISODIUM COCOYL GLUTAMATE, GLYCOLIC ACID, BENTONITE, NIACINAMIDE, SODIUM HYDROXIDE, AZELAIC ACID, CAMELLIA SINENSIS LEAF EXTRACT, TOCOPHEROL, GLYCERIN, ETHYLHEXYLGLYCERIN, POLYDEXTROSE, DEXTRIN, AMYLOPECTIN, SODIUM COCOYL GLUTAMATE, XANTHAN GUM, SODIUM CHLORIDE, CITRIC ACID, POTASSIUM SORBATE, PHENOXYETHANOL, SODIUM BENZOATE

QUESTIONS?

1.866.927.2783

PACKAGE LABEL

148 mL

30 mL